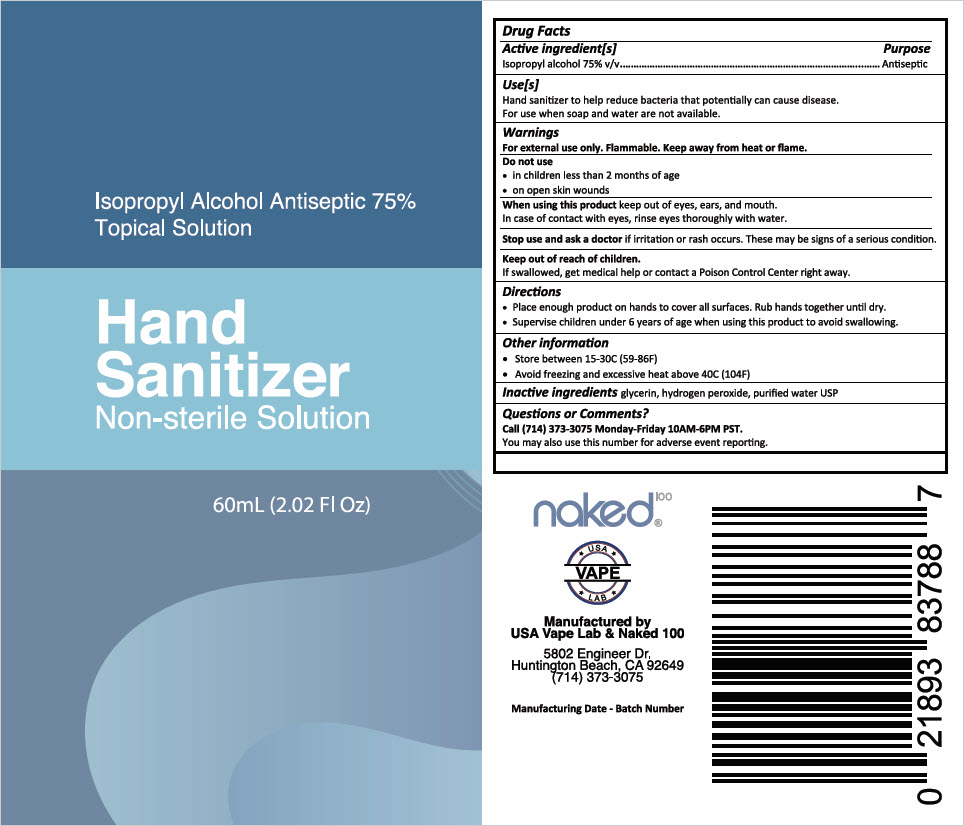 DRUG LABEL: Hand Sanitizer
NDC: 74912-001 | Form: SOLUTION
Manufacturer: SCHWARTZ E LIQUID, THE
Category: otc | Type: HUMAN OTC DRUG LABEL
Date: 20200415

ACTIVE INGREDIENTS: Isopropyl alcohol 75 mL/100 mL
INACTIVE INGREDIENTS: glycerin; hydrogen peroxide; water

Hand Sanitizer

Drug Facts

Active ingredient[s]

Isopropyl alcohol 75% v/v

Purpose

Antiseptic

Use[s]

Hand sanitizer to help reduce bacteria that potentially can cause disease. For use when soap and water are not available.

Warnings

For external use only. Flammable. Keep away from heat or flame

Do not use

- in children less than 2 months of age
- on open skin wounds

When using this product keep out of eyes, ears, and mouth. In case of contact with eyes, rinse eyes thoroughly with water.

Stop use and ask a doctor if irritation or rash occurs. These may be signs of a serious condition.

Keep out of reach of children. If swallowed, get medical help or contact a Poison Control Center right away.

Directions

- Place enough product on hands to cover all surfaces. Rub hands together until dry.
- Supervise children under 6 years of age when using this product to avoid swallowing.

Other information

- Store between 15-30C (59-86F)
- Avoid freezing and excessive heat above 40C (104F)

Inactive ingredients

glycerin, hydrogen peroxide, purified water USP

Questions or Comments?

Call (714) 373-3075 Monday-Friday 10am-6pm PST.

You may also use this number for adverse event reporting.

Manufactured by
USA Vape Lab & Naked 100
5802 Engineer Dr.
Huntington Beach, CA 92649
(714)373-3075

PRINCIPAL DISPLAY PANEL - 60 mL Bottle Label

Isopropyl Alcohol Antiseptic 75%
Topical Solution

Hand
Sanitizer
Non-sterile Solution

60mL (2.02 Fl Oz)